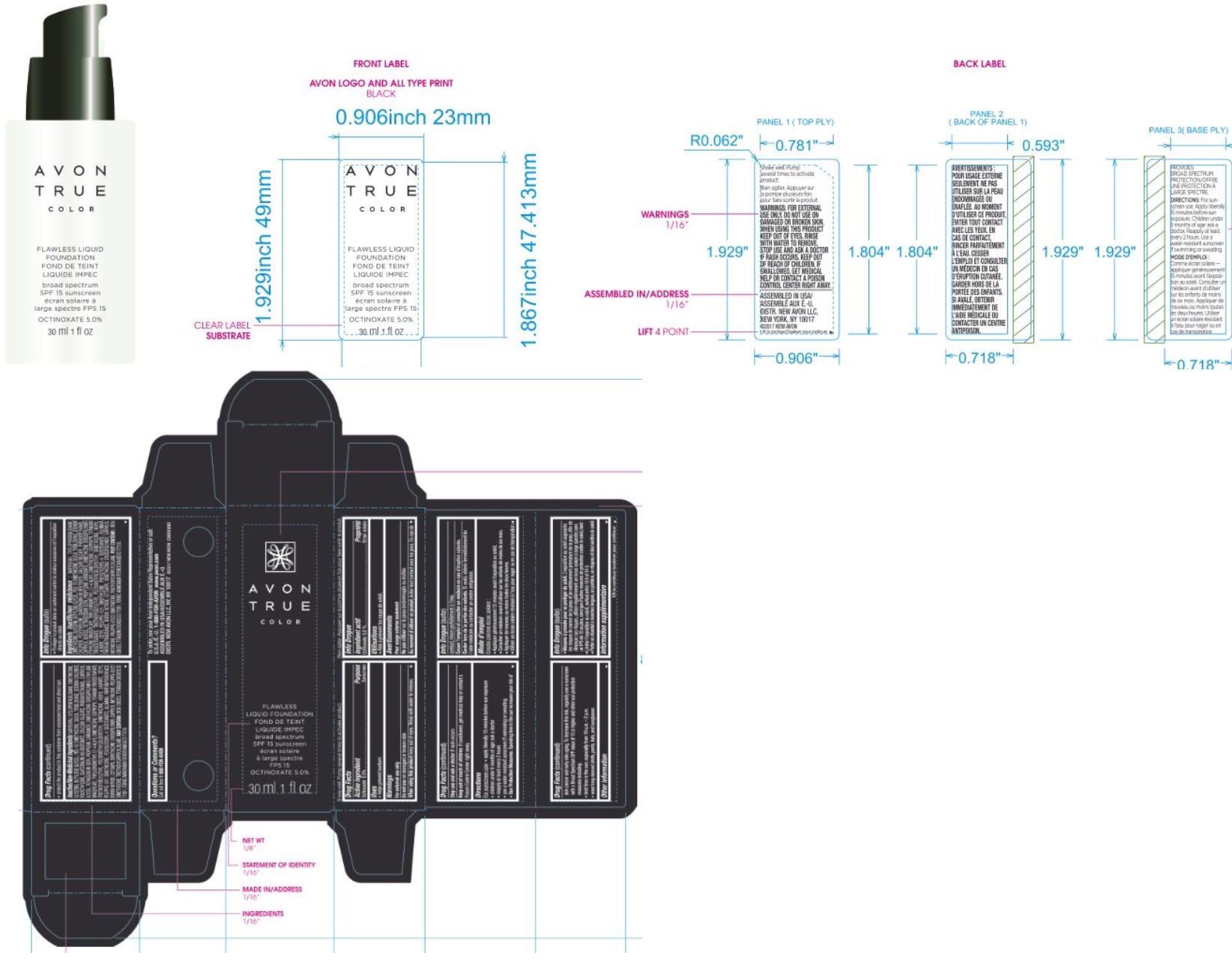 DRUG LABEL: True Color Flawless Liquid Foundation SPF15
NDC: 10096-9506 | Form: LOTION
Manufacturer: New Avon LLC
Category: otc | Type: HUMAN OTC DRUG LABEL
Date: 20180408

ACTIVE INGREDIENTS: OCTINOXATE 5 g/100 g
INACTIVE INGREDIENTS: WATER

True Color Flawless Liquid Foundation SPF15

ACTIVE INGREDIENT

Active Ingredients/Ingrédients actifs:

OCTINOXATE (5.0 %)

INDICATIONS & USAGE

Uses

- helps prevent sunburn

WARNINGS

For external use only

Do not use on damaged or broken skin

When using this product keep out of eyes. Rinse with water to remove.

Stop use and ask a doctor if rash occurs

Keep out of reach of children. If swallowed, get medical help or contact a Poison Control Center right away.

DOSAGE & ADMINISTRATION

Directions

For sunscreen use:

- apply liberally 15 minutes before sun exposure
- children under 6 months of age: ask a doctor
- reapply at least every 2 hours
- use a water resistant sunscreen if swimming or sweating

Sun Protection Measures. Spending time in the sun increases your risk of skin cancer and early skin aging. To decrease this risk, regularly use a sunscreen with a Broad Spectrum SPF value of 15 or higher and other sun protection measures including:

- limit time in the sun, especially from 10 a.m. – 2 p.m.
- wear long-sleeved shirts, pants, hats, and sunglasses

Other Information

- protect the product in this container from excessive heat and direct sun

INACTIVE INGREDIENT

Inactive Ingredients/Ingrédients inactifs: WATER/EAU, CYCLOPENTASILOXANE, DIMETHICONE, GLYCERIN, BUTYLENE GLYCOL, PEG-10 DIMETHICONE, SILICA,TRISILOXANE, SODIUM CHLORIDE, POLYETHYLENE, QUATERNIUM-90 BENTONITE, CALCIUM SILICATE, PHENOXYETHANOL, CAPRYLYL GLYCOL,TETRASODIUM EDTA, PROPYLENE CARBONATE, DIMETHICONE CROSSPOLYMER, ETHYLENE BRASSYLATE, TRIFLUOROMETHYLC1-4 ALKYLDIMETHICONE,ISOPROPYL TITANIUM TRIISOSTEARATE, TRIETHOXYSILYLETHYL POLYDIMETHYLSILOXYETHYL DIMETHICONE, HEXYL LAURATE, CETYL PEG/PPG-10/1 DIMETHICONE, POLYGLYCERYL-4 ISOSTEARATE, ALUMINA, PARFUM/FRAGRANCE, BORON NITRIDE, CETEARYL DIMETHICONE CROSSPOLYMER,CAPRYLYL METHICONE,PEG/PPG-20/23 DIMETHICONE, TRIETHOXYCAPRYLYLSILANE.MAY CONTAIN: IRON OXIDES,TITANIUM DIOXIDE/CI 77891, FERRIC AMMONIUM FERROCYANIDE/CI 77510.

QUESTIONS

Questions or Comments?
Call toll free 1-800-FOR-AVON or 1-800-265-AVON in Canada